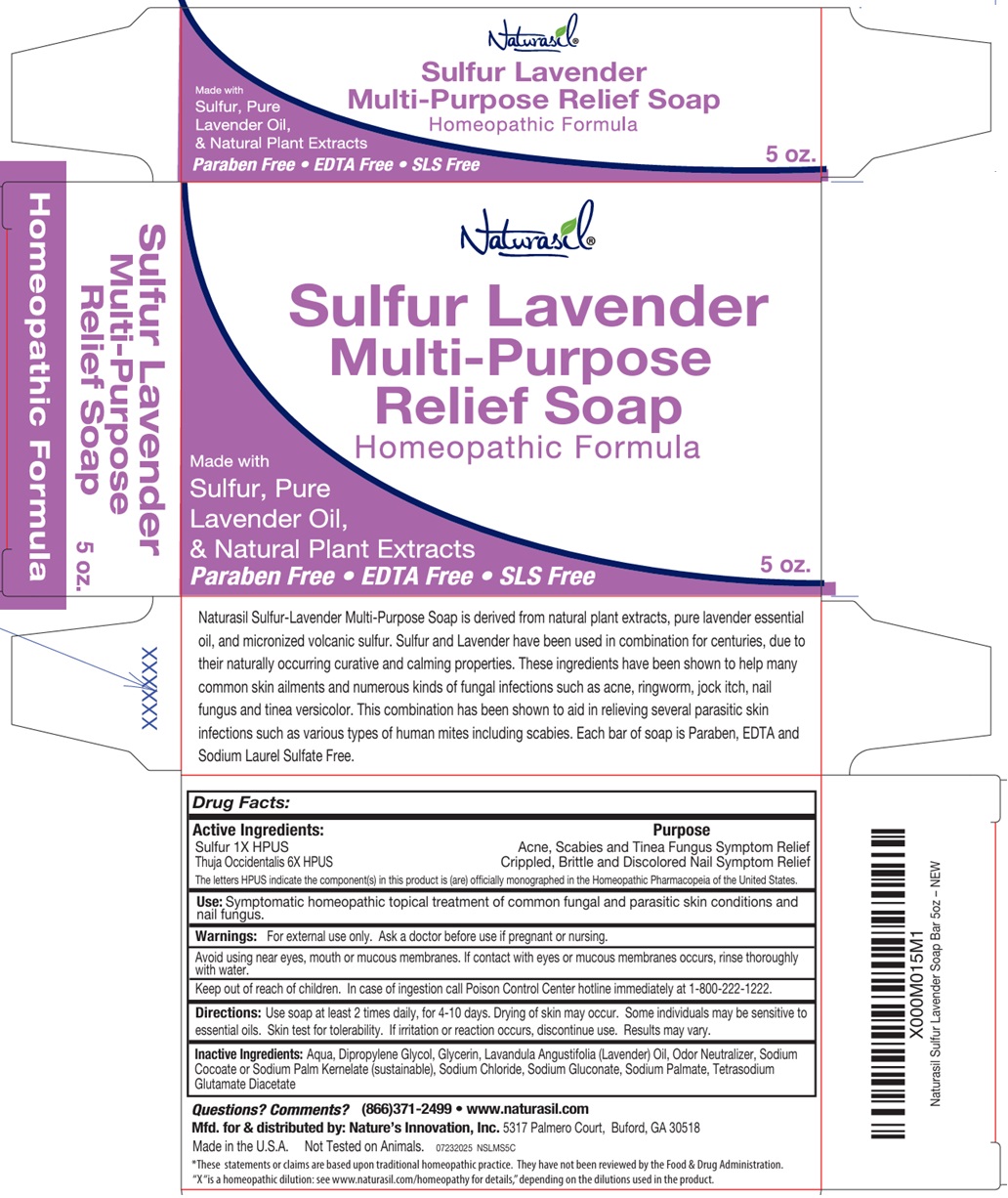 DRUG LABEL: Naturasil
NDC: 10893-600 | Form: SOAP
Manufacturer: Nature's Innovation, Inc.
Category: homeopathic | Type: HUMAN OTC DRUG LABEL
Date: 20251022

ACTIVE INGREDIENTS: SULFUR 1 [hp_X]/1 g; THUJA OCCIDENTALIS LEAFY TWIG 6 [hp_X]/1 g
INACTIVE INGREDIENTS: WATER; DIPROPYLENE GLYCOL; GLYCERIN; LAVENDER OIL; SODIUM COCOATE; SODIUM PALM KERNELATE; SODIUM CHLORIDE; SODIUM GLUCONATE; SODIUM PALMATE; TETRASODIUM GLUTAMATE DIACETATE

Sulfur Lavender Multi-Purpose Relief Soap

Active Ingredients:

Sulfur 1X HPUS
Thuja Occidentalis 6X HPUS

The letters HPUS indicate the component(s) in this product is (are) officially monographed in the Homeopathic Pharmacopeia of the United States.

Purpose

Acne, Scabies and Tinea Fungus Symptom Relief
Crippled, Brittle and Discolored Nail Symptom Relief

Use:

Symptomatic homeopathic topical treatment of common fungal and parasitic skin conditions and nail fungus.

Warnings:

For external use only. Ask a doctor before use if pregnant or nursing.

Avoid using near eyes, mouth or mucous membranes. If contact with eyes or mucous membranes occurs, rinse thoroughly with water.

Keep out of reach of children. In case of ingestion call Poison Control Center hotline immediately at 1-800-222-1222.

Directions:

Use soap at least 2 times daily, for 4-10 days. Drying of skin may occur. Some individuals may be sensitive to essential oils. Skin test for tolerability. If irritation or reaction occurs, discontinue use. Results may vary.

Inactive Ingredients:

Aqua, Dipropylene Glycol, Glycerin, Lavandula Angustifolia (Lavender) Oil, Odor Neutralizer, Sodium Cocoate or Sodium Palm Kernelate (sustainable), Sodium Chloride, Sodium Gluconate, Sodium Palmate, Tetrasodium Glutamate Diacetate

Questions? Comments?

(866)371-2499 • www.naturasil.com

Homeopathic Formula

Made with Sulfur, Pure Lavender Oil & Natural Plant Extracts

Paraben Free • EDTA Free • SLS Free

Naturasil Sulfur-Lavender Multi-Purpose Soap is derived from natural plant extracts, pure lavender essential oil, and micronized volcanic sulfur. Sulfur and Lavender have been used in combination for centuries, due to their naturally occurring curative and calming properties. These ingredients have been shown to help many common skin ailments and numerous kinds of fungal infections such as acne, ringworm, jock itch, nail
fungus and tinea versicolor. This combination has been shown to aid in relieving several parasitic skin infections such as various types of human mites including scabies. Each bar of soap is Paraben, EDTA and Sodium Laurel Sulfate Free.

Mfd. for & distributed by: Nature’s Innovation, Inc. 5317 Palmero Court, Buford, GA 30518
Made in the U.S.A. Not Tested on Animals.

*These statements or claims are based upon traditional homeopathic practice. They have not been reviewed by the Food & Drug Administration.
“X“ is a homeopathic dilution: see www.naturasil.com/homeopathy for details,” depending on the dilutions used in the product.